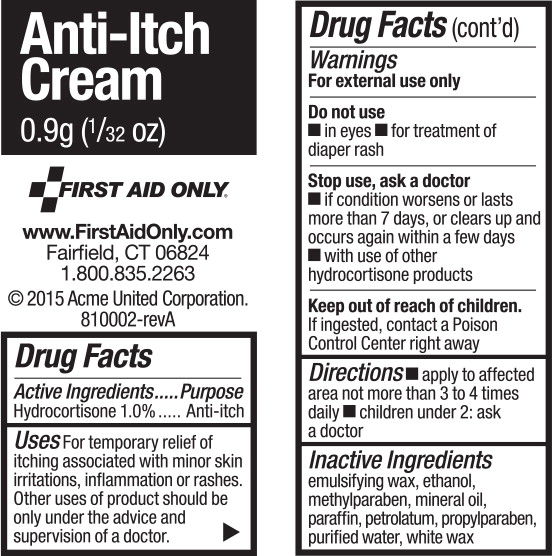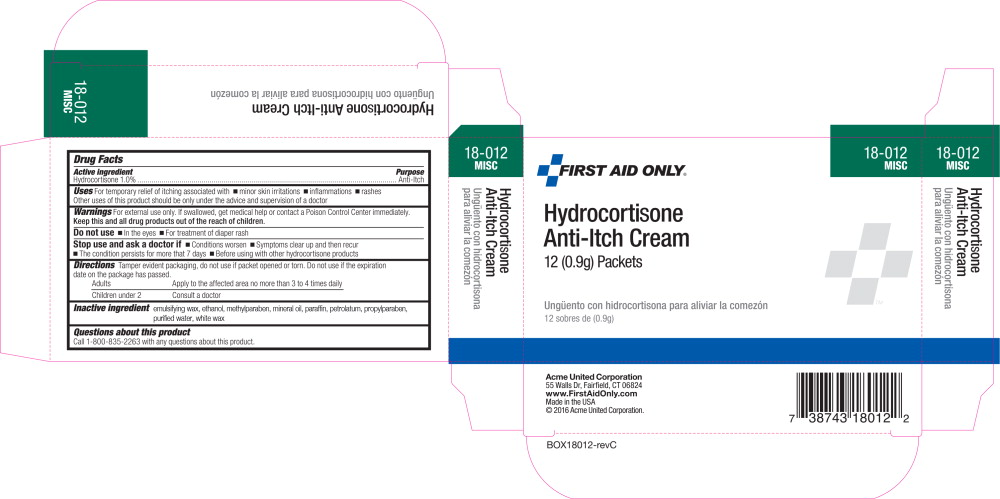 DRUG LABEL: Hydrocortisone
NDC: 0924-1132 | Form: CREAM
Manufacturer: Acme United Corp
Category: otc | Type: HUMAN OTC DRUG LABEL
Date: 20160309

ACTIVE INGREDIENTS: Hydrocortisone 10 mg/1 g
INACTIVE INGREDIENTS: alcohol; methylparaben; mineral oil; paraffin; petrolatum; propylparaben; water; white wax

Drug Facts

Active Ingredients

Hydrocortisone 1.0%

Purpose

Anti-itch

Uses

For temporary relief of itching associated with minor skin irritations, inflammation or rashes.

Other uses of product should be only under the advice of supervision of a doctor.

Warnings

For external use only

Do not use

- in eyes
- for treatment of dipper rash

Stop use, ask a doctor

- if condition worsens or lasts more than 7 days, or clears up and occurs again within a few days
- with use of other hydrocortisone products

Keep out of reach of children.

If ingested, contact a Poison Control Center right away

Directions

- apply to affected area not more than 3 to 5 times daily
- children under 2: as a doctor

Inactive Ingredients

emulsifying wax, ethanol, methylparaben, mineral oil, paraffin, petrolatum, propylparaben, purified water, white wax

Principal Display Panel - 0.9g Carton Label

18-012
MISC

FIRST AID ONLY®

Hydrocortisone
Anti-Itch Cream
12 (0.9g) Packets

Ungüento con hidrocortisona para aliviar la comezón
12 sobres de (0.9g)

Principal Display Panel - 0.9g Packet Label

Anti-Itch
Cream

0.9g (^1/32 oz)

FIRST AID ONLY®

www.FirstAidOnly.com

Fairfield, CT 06824

1.800.835.2263

©2015 Acme United Corporation. 810002-revA